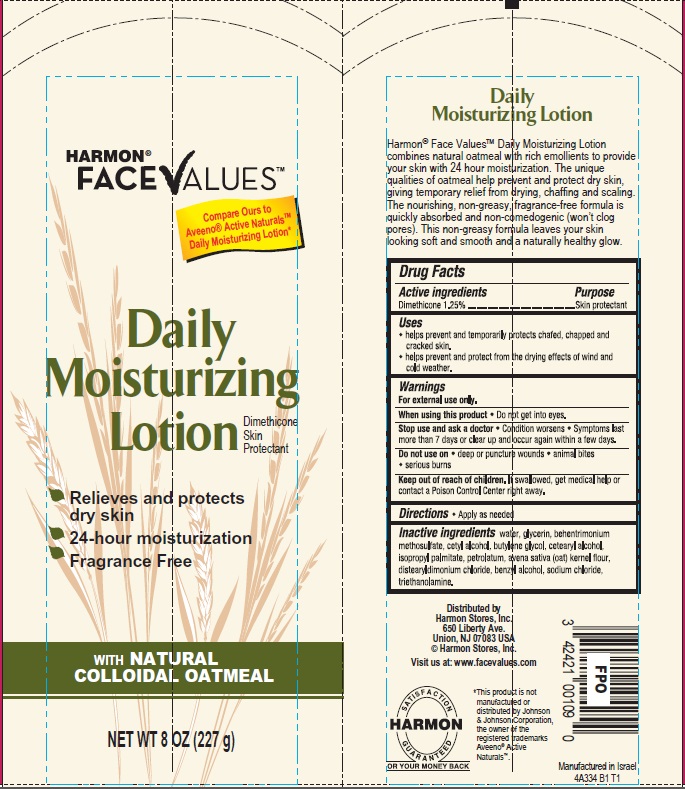 DRUG LABEL: Harmon Face Values Daily Moisturizing
NDC: 63940-334 | Form: LOTION
Manufacturer: Harmon Stores Inc.
Category: otc | Type: HUMAN OTC DRUG LABEL
Date: 20140905

ACTIVE INGREDIENTS: DIMETHICONE 1.25 g/100 mL
INACTIVE INGREDIENTS: WATER; GLYCERIN; BEHENTRIMONIUM METHOSULFATE; CETYL ALCOHOL; BUTYLENE GLYCOL; CETOSTEARYL ALCOHOL; ISOPROPYL PALMITATE; PETROLATUM; OATMEAL; DISTEARYLDIMONIUM CHLORIDE; BENZYL ALCOHOL; SODIUM CHLORIDE; TROLAMINE

Harmon® Face Values™ Daily Moisturizing Lotion

Active ingredient

Dimethicone 1.25%

Purpose

Skin protectant

Uses

- helps prevent and temporarily protects chafed, chapped and cracked skin.
- helps prevent and protect from the drying effects of wind and cold weather.

Warnings

For external use only.

When using this product

- Do not get into eyes.

Stop use and ask a doctor

- Condition worsens
- Symptoms last more than 7 days or clear up and occur again within a few days.

Do not use on

- deep or puncture wounds
- animal bites
- serious burns

Keep Out of Reach of Children.

If swallowed, get medical help or contact a Poison Control Center right away.

Directions

- Apply as needed

Inactive ingredients

water, glycerin, behentrimonium methosulfate, cetyl alcohol, butylene glycol, cetearyl alcohol, isopropyl palmitate, petrolatum, avena sativa (oat) kernel flour, distearyldimonium chloride, benzyl alcohol, sodium chloride, triethanolamine.

Package/Label Principal Display Panel

Harmon®
FACE VALUES™

Compare Ours to Aveeno® Active Naturals™ Daily Moisturizing Lotion*

Daily
Moisturizing
Lotion
Dimethicone Skin Protectant

Relieves and protects dry skin

24-hour moisturization

Fragrance Free

with NATURAL COLLOIDAL OATMEAL

NET WT 8 OZ (227 g)

Daily Moisturizing Lotion

Harmon® Face Values™ Daily Moisturizing Lotion combines natural oatmeal with rich emollients to provide your skin with 24 hour moisturization. The unique qualities of oatmeal help prevent and protect dry skin, giving temporary relief from drying, chaffing and scaling. The nourishing, non-greasy fragrance-free formula is quickly absorbed and non-comedogenic (won’t clog pores). This non-greasy formula leaves your skin looking soft and smooth and a naturally healthy glow.

Distributed by
Harmon Stores, Inc.
650 Liberty Ave.
Union, NJ 07083 USA
© Harmon Stores, Inc.

Visit us at: www.facevalues.com

SATISFACTION GUARANTEED
OR YOUR MONEY BACK

*This product is not manufactured or distributed by Johnson & Johnson Corporation, the owner of the registered trademarks Aveeno® Active Naturals™.

Manufactured in Israel
4A334 B1 T1

Carton Label